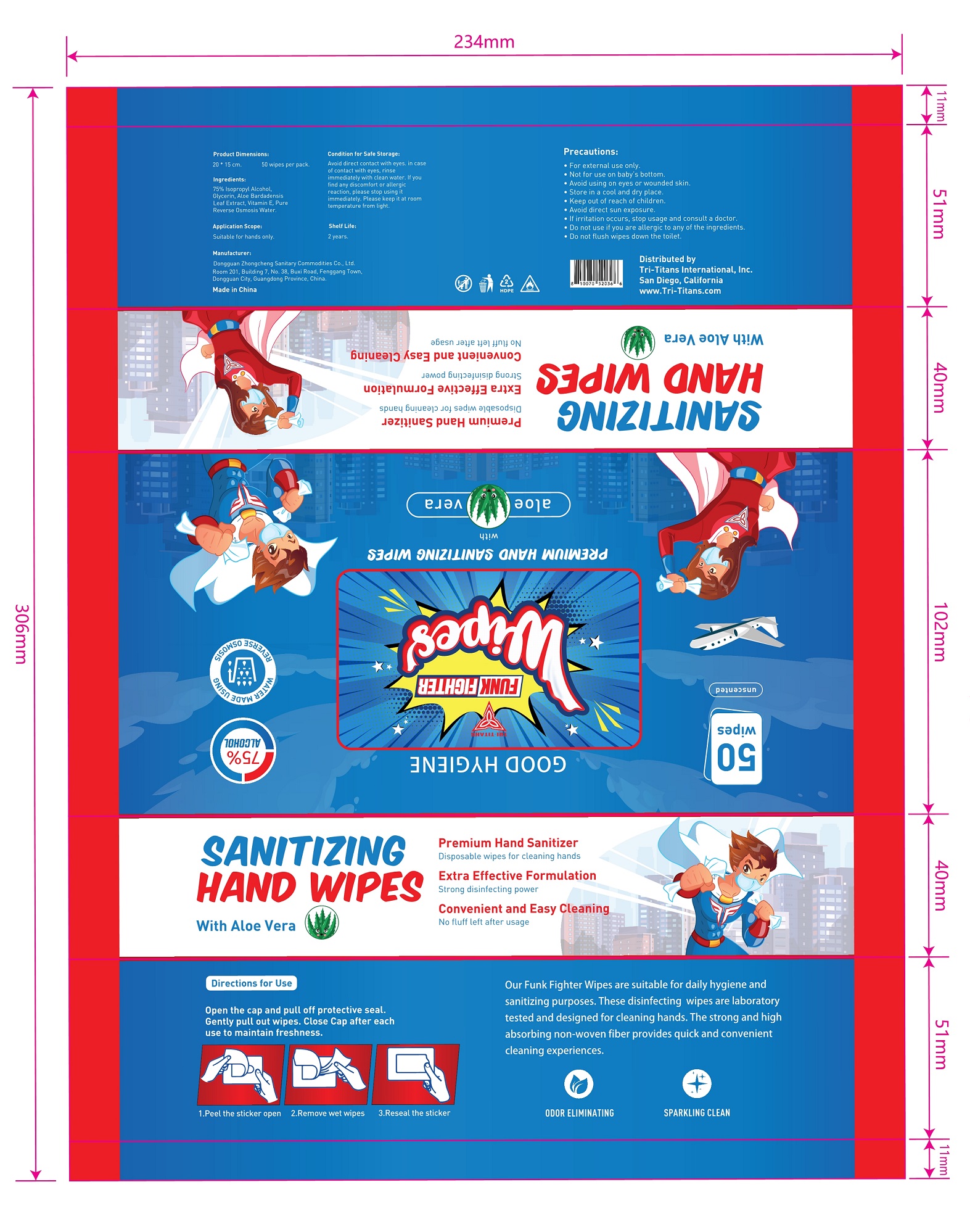 DRUG LABEL: Tri-Titans Funk Fighter Hand Sanitizing Wipes
NDC: 55482-058 | Form: CLOTH
Manufacturer: Dongguan Zhongcheng Sanitary Commodities Co., Ltd.
Category: otc | Type: HUMAN OTC DRUG LABEL
Date: 20210428

ACTIVE INGREDIENTS: ISOPROPYL ALCOHOL 75 mL/100 mL
INACTIVE INGREDIENTS: GLYCERIN; ALOE; WATER; .ALPHA.-TOCOPHEROL

55482-058 Tri-Titans Funk Fighter Hand Sanitizing Wipes 50WIPES

Active Ingredient(s)

ISOPROPYL ALCOHOL 75%

Purpose

Antiseptic,Wipes

Use

Open the cap and pull off protective seal. Gently pull out wipes. Close cap after each use to maintain freshness.

1.Peel the sticker open.

2.Remove wet wipes.

3.Reseal the sticker.

Warnings

- For external use only.
- Not for use on baby's bottom.
- Avoid using on eyes or wounded skin.
- Store in a cool and dry place.
- Keep out of reach of children.
- Avoid direct sun exposure.
- If irritation occurs, stop usage and consult a doctor.
- Do not use if you are allergic to any of the ingredients.
- Do not flush wipes down the toilet.

Do not use

- If irritation occurs, stop usage and consult a doctor.
  Do not use if you are allergic to any of the ingredients.
  Do not flush wipes down the toilet.
- Suitable for hands only.

WHEN USING

For external use only.
Not for use on baby's bottom.
Avoid using on eyes or wounded skin.
Store in a cool and dry place.
Keep out of reach of children.
Avoid direct sun exposure.
If irritation occurs, stop usage and consult a doctor.
Do not use if you are allergic to any of the ingredients.
Do not flush wipes down the toilet.

For external use only.
Not for use on baby's bottom.
Avoid using on eyes or wounded skin.
Store in a cool and dry place.
Keep out of reach of children.
Avoid direct sun exposure.
If irritation occurs, stop usage and consult a doctor.
Do not use if you are allergic to any of the ingredients.
Do not flush wipes down the toilet.

Keep out of reach of children. If swallowed, get medical help or contact a Poison Control Center right away.

Directions

Our Funk Fighter Wipes are suitable for daily hygiene and sanitizing
purposes. These sanitizing wipes are laboratory tested and designed
for cleaning hands. The strong and high absorbing non-woven fiber provides quick and convenient cleaning experiences.

Other information

- AVOID DIRECT CONTACT WITH EYES.
- IN CASE OF CONTACT WITH EYES,RINSE IMMEDIATELY WITH CLEAN WATER.
- IF YOU FIND ANY DISCOMFORT OR ALLERGIC REACTION,PLEASE STOP USING IT IMMEDIATELY.
- PLEASE KEEP IT AT ROOM TEMPERTURE FROM LIGHT.
- Shelf Life:2 years.

Inactive ingredients

Isopropyl Alcohol, Glycerin, Aloe Bardadensis Leaf Extract, Vitamin E, Water

Package Label - Principal Display Panel

50 wipes NDC:55482-058-01